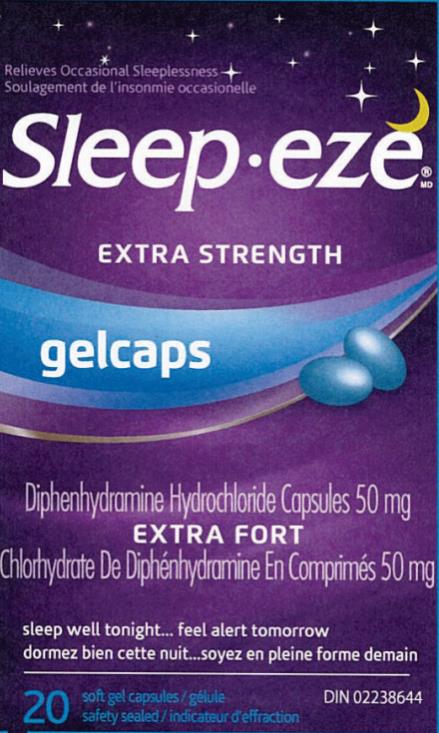 DRUG LABEL: Sleepeze Gelcaps
NDC: 63029-927 | Form: CAPSULE, GELATIN COATED
Manufacturer: Medtech Products Inc.
Category: otc | Type: HUMAN OTC DRUG LABEL
Date: 20240118

ACTIVE INGREDIENTS: DIPHENHYDRAMINE HYDROCHLORIDE 50 mg/1 1
INACTIVE INGREDIENTS: FD&C BLUE NO. 1; GELATIN; GLYCERIN; POLYETHYLENE GLYCOL, UNSPECIFIED; SORBITOL; WATER

SleepEze Gelcaps 50 mg_Export only 63029-927-20

Drug Facts

Active ingredient (in each capsule)

Diphenhydramine Hydrochloride 50 mg

Purpose

Nighttime sleep aid

Uses

● relieves occasional sleeplessness

Warnings

Do not use

●if you are elderly, as this drug may cause excitation rather than sedation ●with any other product containing diphenhydramine, even one used on skin ●in children under 12 years of age

Ask a doctor or pharmacist before use if you

●have ▪a breathing problem such as emphysema or chronic bronchitis ▪glaucoma ▪difficulty urinating ●take sedatives or tranquilizers ●are pregnant or breastfeeding

When using this product

avoid drinking alcohol.

Stop use and ask a doctor if

sleeplessness continues for more than 2 weeks. Sleeplessness may be a symptom of a serious underlying medical illness.

Keep out of reach of children.

In case of overdose, call a poison control centre or get medical help right away.

Directions

Adults and children 12 years and over: ▪take 1 capsule at bedtime if needed, or as directed by a doctor ▪if you feel drowsy in the morning, consult a doctor or pharmacist as you may require a lower dosage (25 mg) ▪do not take more than directed

Other information

▪ Store at 20° to 25°C

Inactive ingredients

FD&C blue no. 1, gelatin, glycerin, polyethylene glycol, sorbitan, sorbitol, water

Questions?

1-800-443-4908

.

PRINCIPAL DISPLAY PANEL

Sleep•eze® MD
extra strength
gelcaps
DIPHENHYDRAMINE HYDROCHLORIDE CAPSULES 50 mg
20 soft gel capsules

DIN 02238644